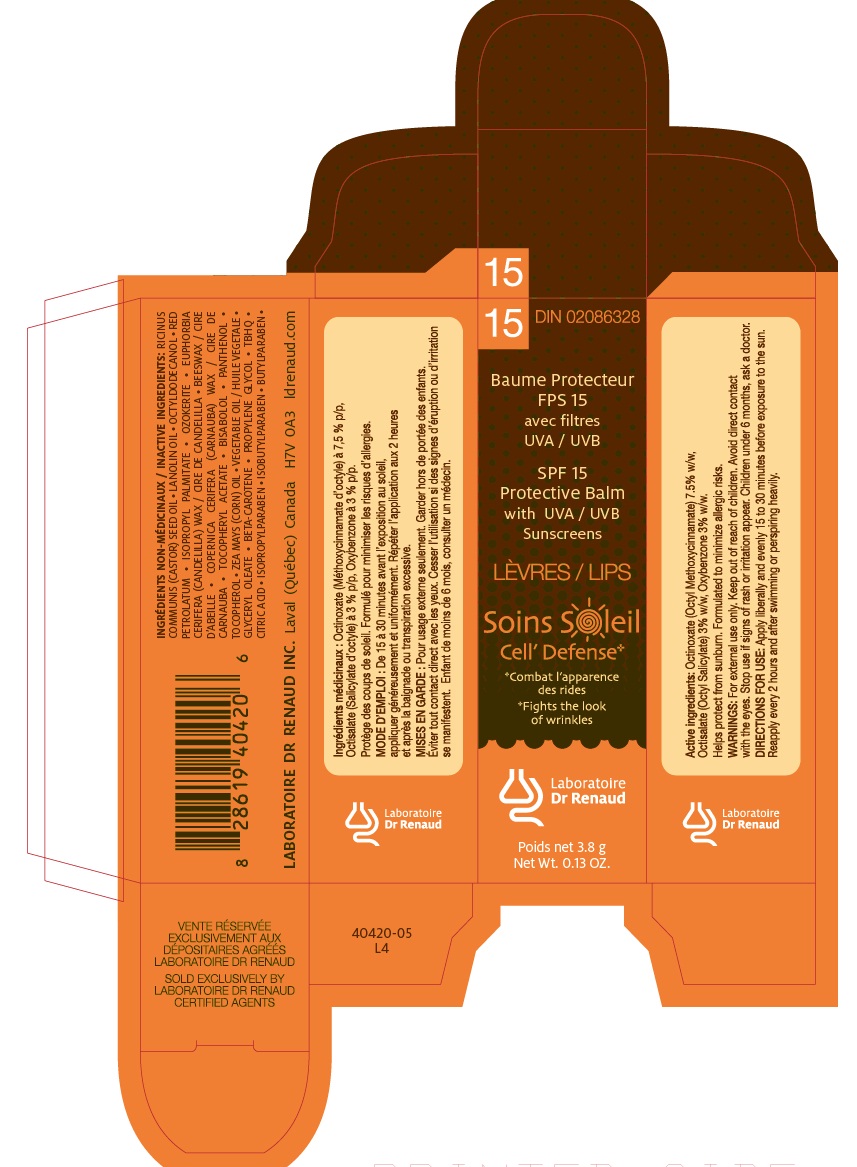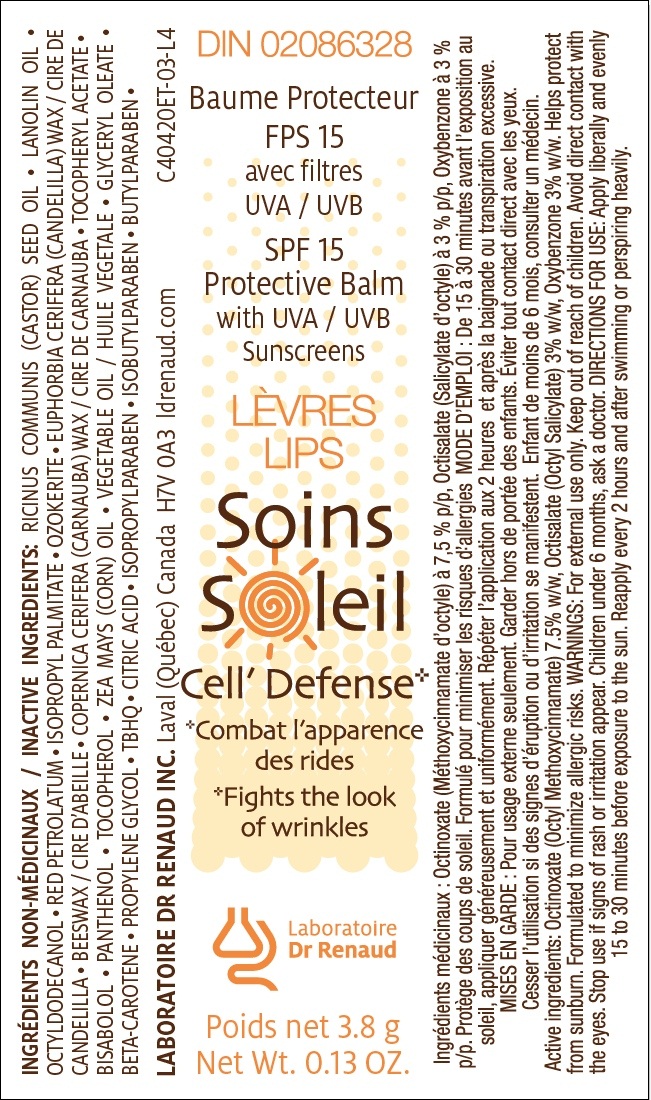 DRUG LABEL: SPF 15 Protective Balm with UVA/UVB Sunscreens
NDC: 62499-420 | Form: STICK
Manufacturer: Laboratoire Dr Renaud inc.
Category: otc | Type: HUMAN OTC DRUG LABEL
Date: 20110323

ACTIVE INGREDIENTS: OCTINOXATE 7.5 g/100 g; OCTISALATE 3 g/100 g; OXYBENZONE 3 g/100 g
INACTIVE INGREDIENTS: RICINUS COMMUNIS SEED; LANOLIN; OCTYLDODECANOL; PETROLATUM; ISOPROPYL PALMITATE; CERESIN; CANDELILLA WAX; YELLOW WAX; CARNAUBA WAX; ACETATE ION; LEVOMENOL; PANTHENOL; ISOPROPYLPARABEN; ISOBUTYLPARABEN; BUTYLPARABEN; ALPHA-TOCOPHEROL; CORN OIL; SUNFLOWER OIL; T-BUTYLHYDROQUINONE; GLYCERYL MONOOLEATE; BETA CAROTENE; PROPYLENE GLYCOL; CITRIC ACID MONOHYDRATE

Drug Facts

ACTIVE INGREDIENT

Octinoxate (Octyl Methoxycinnamate) à 7.5 % w/w, Octisalate (Octyl Salicylate) à 3% w/w, Oxybenzone à 3% w/w.

Inactive ingredients

RICINUS COMMUNIS (CASTOR) SEED OIL • LANOLIN OIL • OCTYLDODECANOL • RED PETROLATUM • ISOPROPYL PALMITATE • OZOKERITE • EUPHORBIA CERIFERA (CANDELILLA) WAX / CIRE DE CANDELILLA • BEESWAX / CIRE D’ABEILLE • COPERNICA CERIFERA (CARNAUBA) WAX / CIRE DE CARNAUBA • TOCOPHERYL ACETATE • BISABOLOL • PANTHENOL • TOCOPHEROL • ZEA MAYS (CORN) OIL • VEGETABLE OIL / HUILE VEGETALE • GLYCERYL OLEATE • BETA-CAROTENE • PROPYLENE GLYCOL • TBHQ • CITRIC ACID • ISOPROPYLPARABEN • ISOBUTYLPARABEN • BUTYLPARABEN •

PURPOSE

Helps protect from sunburn.Formulated to minimize allergic risks.

DOSAGE AND ADMINISTRATION

Apply liberally and evenly 15 to 30 minutes before exposure to the sun.Reapply every 2 hours and after swimming perspiring heavily.

image of cartridge label
image of carton label

WARNINGS

For external use only.Keep out of children. Avoid direct contact with the eyes. Stop use if signs of rash or irritation appear.Children under 6 months, ask doctor.